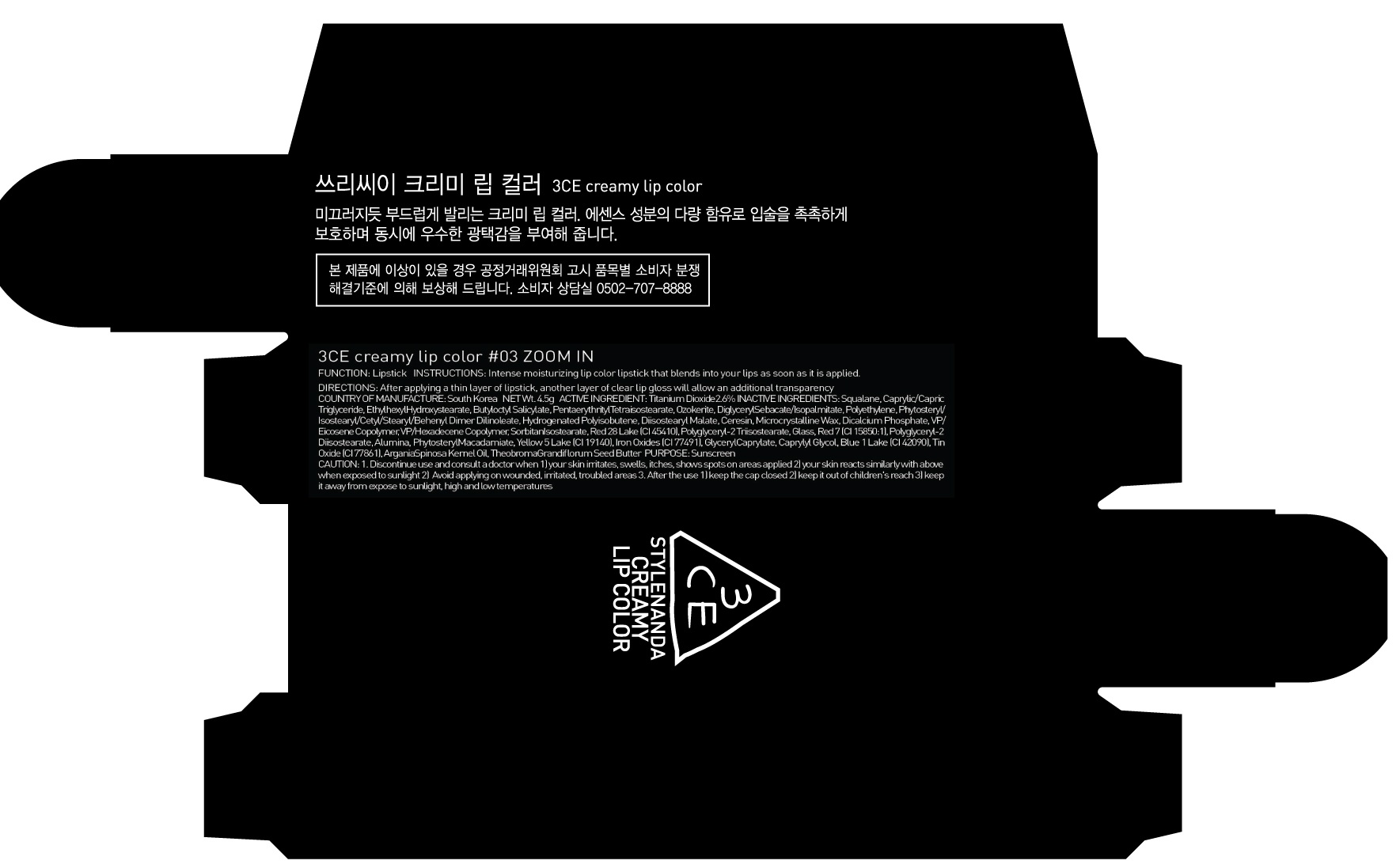 DRUG LABEL: 3CE CRE AMY LIP COLOR 03 ZOOM IN
NDC: 60764-113 | Form: LIPSTICK
Manufacturer: Nanda Co., Ltd
Category: otc | Type: HUMAN OTC DRUG LABEL
Date: 20161014

ACTIVE INGREDIENTS: Titanium Dioxide 0.11 g/4.5 g
INACTIVE INGREDIENTS: Squalane; Ethylhexyl Hydroxystearate

ACTIVE INGREDIENT

Active Ingredient: Titanium Dioxide 2.6%

INACTIVE INGREDIENT

Inactive Ingredients: Squalane, Caprylic/Capric Triglyceride, Ethylhexyl Hydroxystearate, Butyloctyl Salicylate, PentaerythritylTetraisostearate, Ozokerite, DiglycerylSebacate/Isopalmitate, Polyethylene, Phytosteryl/Isostearyl/Cetyl/Stearyl/Behenyl Dimer Dilinoleate, Hydrogenated Polyisobutene, Diisostearyl Malate, Ceresin, Microcrystalline Wax, Dicalcium Phosphate, VP/Eicosene Copolymer, VP/Hexadecene Copolymer, SorbitanIsostearate, Red 28 Lake (CI 45410), Polyglyceryl-2 Triisostearate, Glass, Red 7 (CI 15850:1), Polyglyceryl-2 Diisostearate, Alumina, PhytosterylMacadamiate, Yellow 5 Lake (CI 19140), Iron Oxides (CI 77491), GlycerylCaprylate, Caprylyl Glycol, Blue 1 Lake (CI 42090), Tin Oxide (CI 77861), ArganiaSpinosa Kernel Oil, TheobromaGrandiflorum Seed Butter

PURPOSE

Purpose: Sunscreen

CAUTION

CAUTION: 1. Discontinue use and consult a doctor when - your skin irritates, swells, itches, shows spots on areas applied - your skin reacts similarly with above when exposed to sunlight 2. Avoid applying on wounded, irritated, troubled areas 3. After the use - keep the cap closed - keep it out of children's reach - keep it away from expose to sunlight, high and low temperatures

DESCRIPTION

INSTRUCTIONS: Intense moisturizing lip color lipstick that blends into your lips as soon as it is applied.

Directions: After applying a thin layer of lipstick, another layer of clear lip gloss will allow an additional transparency